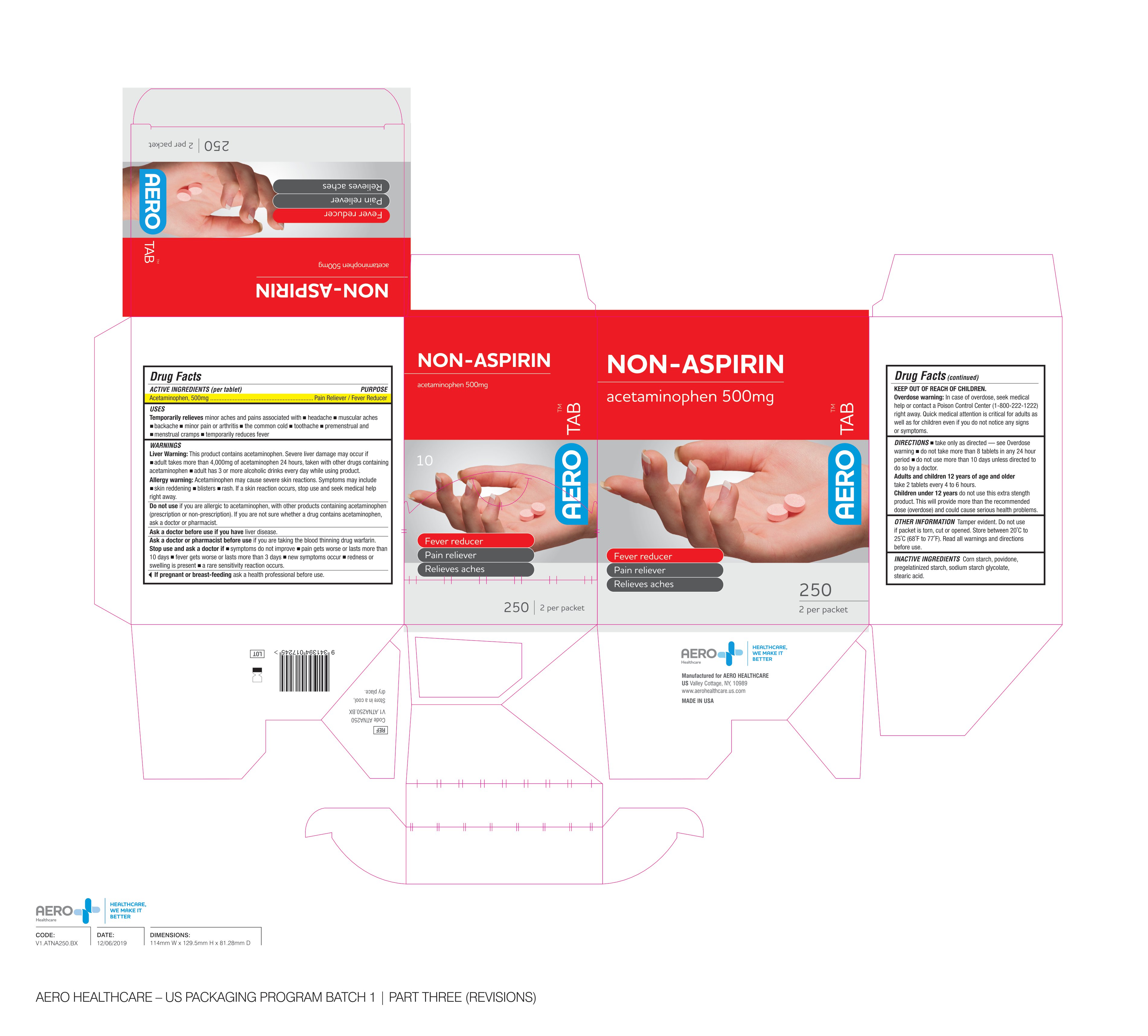 DRUG LABEL: AeroTab Non-Aspirin
NDC: 55305-126 | Form: TABLET
Manufacturer: Aero Healthcare
Category: otc | Type: HUMAN OTC DRUG LABEL
Date: 20250226

ACTIVE INGREDIENTS: ACETAMINOPHEN 500 mg/1 1
INACTIVE INGREDIENTS: POVIDONE; STEARIC ACID; STARCH, CORN; SODIUM STARCH GLYCOLATE TYPE A CORN

Aerotab Non-Aspirin Tablets

ACTIVE INGREDIENT

Acteminophen 500 mg

PURPOSE

Pain reliever / fever reducer

USES

temporary relief of minor aches and pains associated with

- common cold
- headache
- toothache
- muscular aches
- backache
- arthritis
- menstrual cramps
- temporarily reduces fever

WARNINGS

Liver Warning: This product contains acetaminophen. Severe liver damage may occur if

- adult takes more than 4000 mg of acetaminophen in 24 hours
- taken with other drugs containing acetaminophen
- adult has 3 or more alcoholic drinks every day while using this product

Allergy Warning: Acetaminophen may cause severe skin reactions. Symptoms may include:

- skin reddening
- blisters
- rash

If a skin reaction occurs, stop use and seek medical help right away.

Do not use

- if you are allergic to acetaminophen
- with any other drug containing acetaminophen (prescription or nonprescription).

If you are not sure whether a drug contains acetaminophen, ask a doctor or pharmacist.

Ask a doctor before use if you have liver disease.

Ask a doctor or pharmacist before use if you are

taking the blood thinning drug warfarin.

Stop use and ask a doctor if

- symptoms do not improve
- pain gets worse or lasts for more than 10 days
- fever gets worse or lasts for more than 3 days
- new symptoms occur
- redness or swelling is present
- a rare sensitivity reaction occurs

If pregnant or breast-feeding

ask a health professional before use.

Keep out of reach of children

In case of accidental overdose, contact a doctor or Poison Control Center (1-800-222-1222) right away. Quick medical attention is critical for adults as well as for children even if you do not notice any signs or symptoms.

DIRECTIONS

- take only as directed - see Overdose warning
- do not take more than 8 tablets in any 24 hour period
- do not use more than 10 days unless directed to do so by a doctor

Adults and children 12 years and over: take 2 tablets every 4 to 6 hours.

Children under 12 years of age: do not use this extra strength product. This will provide more than the recommended dose (overdose) and could cause serious health problems.

OTHER INFORMATION

Tamper evident. Do not use if packet is torn, cut or opened. Store between 20°-25°C (68°-77°F). Read all warnings and directions before use.

INACTIVE INGREDIENTS

corn starch, povidone, pregelatinized starch, sodium starch glycolate, stearic acid

Non Aspirin Tablet

AEROTAB

Non-Aspirin

acetaminophen 500mg

Fever reducer

Pain Reliever

Relieves aches

2 per packet